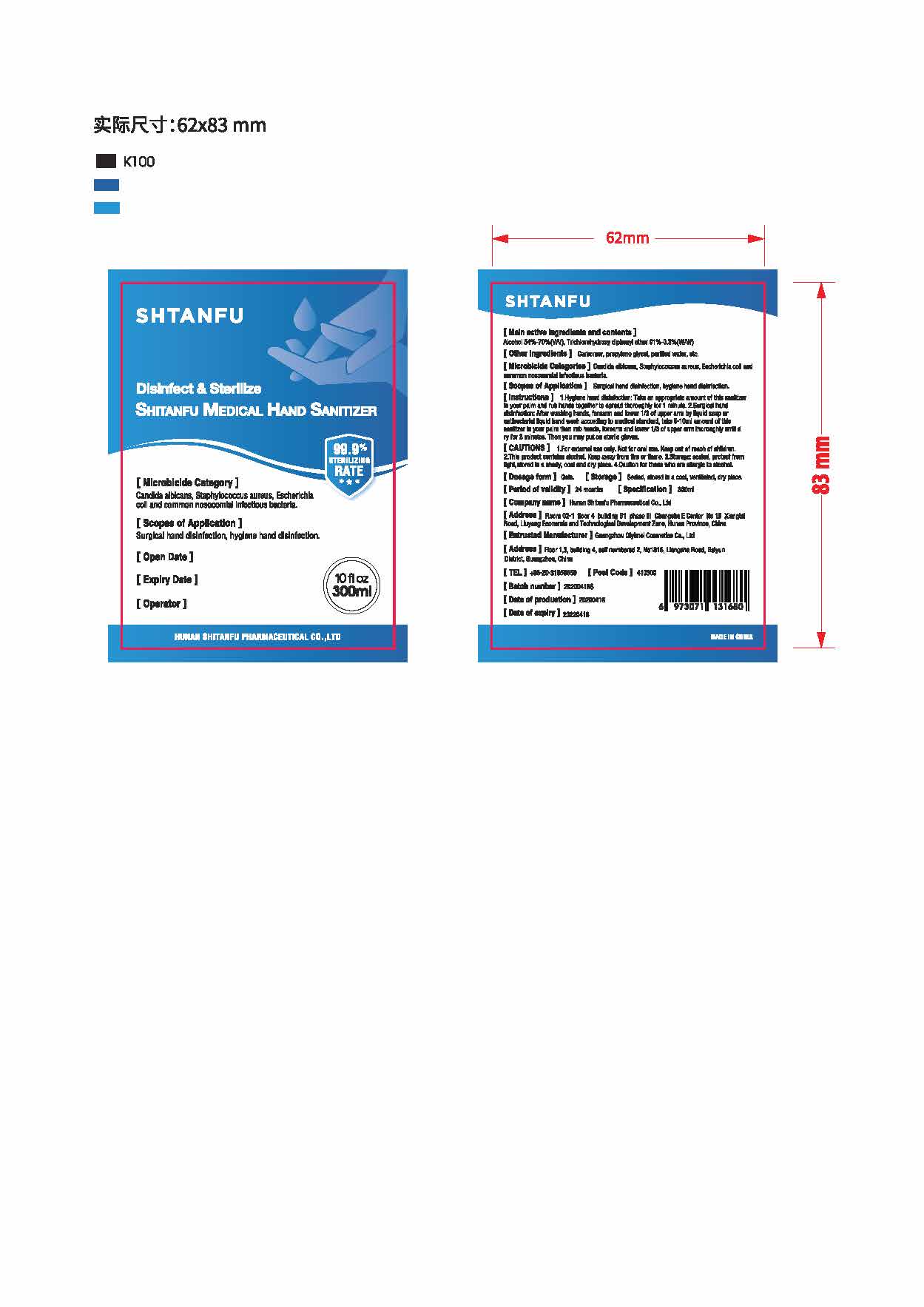 DRUG LABEL: Hand Sanitizer
NDC: 78479-002 | Form: GEL
Manufacturer: Guangzhou Qiyimei Cosmetics co.,ltd
Category: otc | Type: HUMAN OTC DRUG LABEL
Date: 20201229

ACTIVE INGREDIENTS: ALCOHOL 60 mL/100 mL
INACTIVE INGREDIENTS: CARBOMER 940; WATER; TRICLOSAN; PROPANEDIOL

Guangzhou Qiyimei Cosmetics co.,ltd

Active Ingredient(s)

Alcohol 60% v/v. Purpose: Antiseptic

Purpose

Antiseptic, Hand Sanitizer

Use

Surgical hand disinfection, hygiene hand disinfection

Warnings

For external use only. Not for oral use. Keep out of reach of children. This product contains alcohol. Keep awway from fire or flame. Sotorage sealed, protect from light, stored in a shady, cool and dry place. Caution for those who are allergic to alcohol.

Do not use

- in children less than 2 months of age
- on open skin wounds

When using this product keep out of eyes, ears, and mouth. In case of contact with eyes, rinse eyes thoroughly with water.
Stop use and ask a doctor if irritation or rash occurs. These may be signs of a serious condition.
Keep out of reach of children. If swallowed, get medical help or contact a Poison Control Center right away.

Stop use and ask a doctor if irritation or rash occurs. These may be signs of a serious condition.

Keep out of reach of children.

Directions

- Take an appopriate amount of this sanitizer in your palm and rub hands together to spread thoroughly for 1 minute.

Other information

- Sealed, stored in a cool, ventilated dry place.

Inactive ingredients

Carbomer, propylene glycol, water, triclosan

RECENT MAJOR CHANGES

None

Package Label - Principal Display Panel

300mL NDC: 78479-001-01 NOT FOR RESALE - PERSONAL USE ONLY